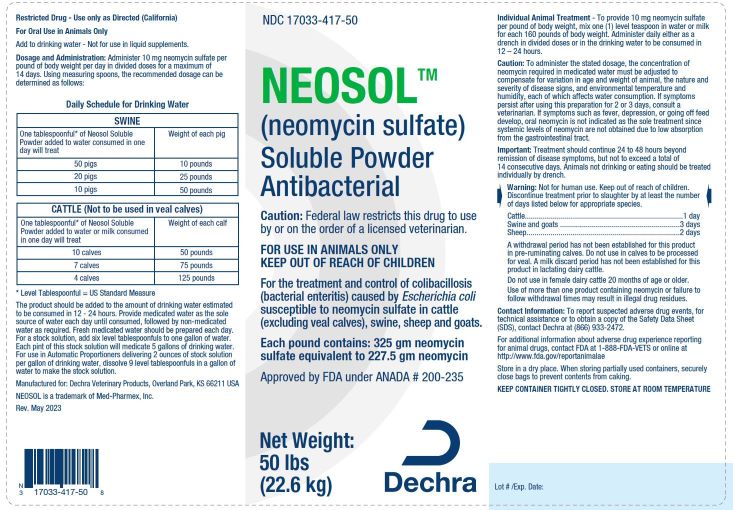 DRUG LABEL: NEOSOL
NDC: 17033-417 | Form: POWDER, FOR SOLUTION
Manufacturer: Dechra Veterinary Products
Category: animal | Type: PRESCRIPTION ANIMAL DRUG LABEL
Date: 20230517

ACTIVE INGREDIENTS: NEOMYCIN SULFATE 50 g/100 g

NEOSOL SOLUBLE POWDER

DESCRIPTION

Neomycin Sulfate

Antibacterial

Approved by FDA under ANADA # 200-235

CAUTION: Federal law restricts this drug to use by or on the order of a licensed veterinarian.

Indicated for the treatment and control of colibacillosis (bacterial enteritis) caused by Escherichia coli susceptible to neomycin sulfate in cattle (excluding veal calves), swine, sheep and goats.

Each pound contains: 325 gm neomycin sulfate equivalent to 227.5 gm neomycin.

Net Weight: 50 lb. (22.6 kg)

Restricted Drug – Use only as Directed (California)

For Oral Use in Animals Only

Add to drinking water – Not for use in liquid supplements.

DOSAGE AND ADMINISTRATION:

Administer 10 mg neomycin sulfate per pound of body weight, per day, in divided doses for a maximum of 14 days.

Net Weight 50 lb. (22.6kg) Container:

Using measuring spoons, the recommended dosage can be determined as follows:

Daily Schedule for Drinking Water

SWINE
One tablespoonful* of Neosol; Solubel Powder added to water; consumed in one day will treat | Weight of each pig
50 pigs | 10 pounds
20 pigs | 25 pounds
10 pigs | 50 pounds

CATTLE (Not to be used in veal calves)
One tablespoonful* of Neosol Solubel Powder added to water or milk consumed in one day will treat | Weight of calf
10 calves | 50 pounds
7 calves | 75 pounds
4 calves | 125 pounds

* Level Tablespoonful = US Standard Measure

The product should be added to the amount of drinking water estimated to be consumed in 12-24 hours. Provide medicated water as the sole source of water each day until consumed, followed by non-medicated water as required. Fresh medicated water should be prepared each day. For a stock solution, add six level tablespoonfuls to one gallon of water. Each pint of this stock solution will medicate 5 gallons of drinking water. For use in Automatic Proportioners delivering 2 ounces of stock solution per gallon of drinking water, dissolve 9 level tablespoonfuls in a gallon of water to make the stock solution.

Individual Animal Treatment: To provide 10 mg neomycin sulfate per pound of body weight, mix one (1) level teaspoon in water or milk for each 160 pounds body weight. Administer daily either as a drench in divided doses or in the drinking water to be consumed in 12-24 hours.

PRECAUTIONS

CAUTION: To administer the stated dosage, the concentration of neomycin required in medicated water must be adjusted to compensate for variation in age and weight of animal, the nature and severity of disease signs, and environmental temperature and humidity, each of which affects water consumption. If symptoms persist after using this preparation for 2 or 3 days, consult a veterinarian. If symptoms such as fever, depression, or going off feed develop, oral neomycin is not indicated as the sole treatment since systemic levels of neomycin are not obtained due to low absorption from the gastrointestinal tract

Important: Treatment should continue 24 to 48 hours beyond remission of disease symptoms, but not to exceed a total of 14 consecutive days. Animals not drinking or eating should be treated individually by drench.

WARNINGS AND PRECAUTIONS

WARNINGS: Not for human use. Keep out of reach of children.

Discontinue treatment prior to slaughter by at least the number of days listed below for appropriate species:

Cattle...........................1 day

Swine and goats...........3 days

Sheep..........................2 days

A withdrawal period has not been established for this product in pre-ruminating calves. Do not use in calves to be processed for veal. A milk discard period has not been established for this product in lactating dairy cattle.

Do not use in female dairy cattle 20 months of age or older.

Use of more than one product containing neomycin or failure to follow withdrawal times may result in illegal drug residue.

CONTACT INFORMATION: To report suspected adverse drug events, for technical assistance or to obtain a copy of the Safety Data Sheet (SDS), contact Dechra at (866) 933-2472. For additional information about adverse drug experience reporting for animal drugs, contact FDA at 1-888-FDA-VETS or online at http://www.fda.gov/reportanimalae

STORAGE AND HANDLING

STORAGE: Store at room temperature. Keep Container Tightly Closed.

Important: Store in a dry place. When storing partially used containers, securely close bags to prevent contents from caking.

Manufactured for:
Dechra Veterinary Products, LLC
Overland Park, KS 66211

Rev. 05/2023